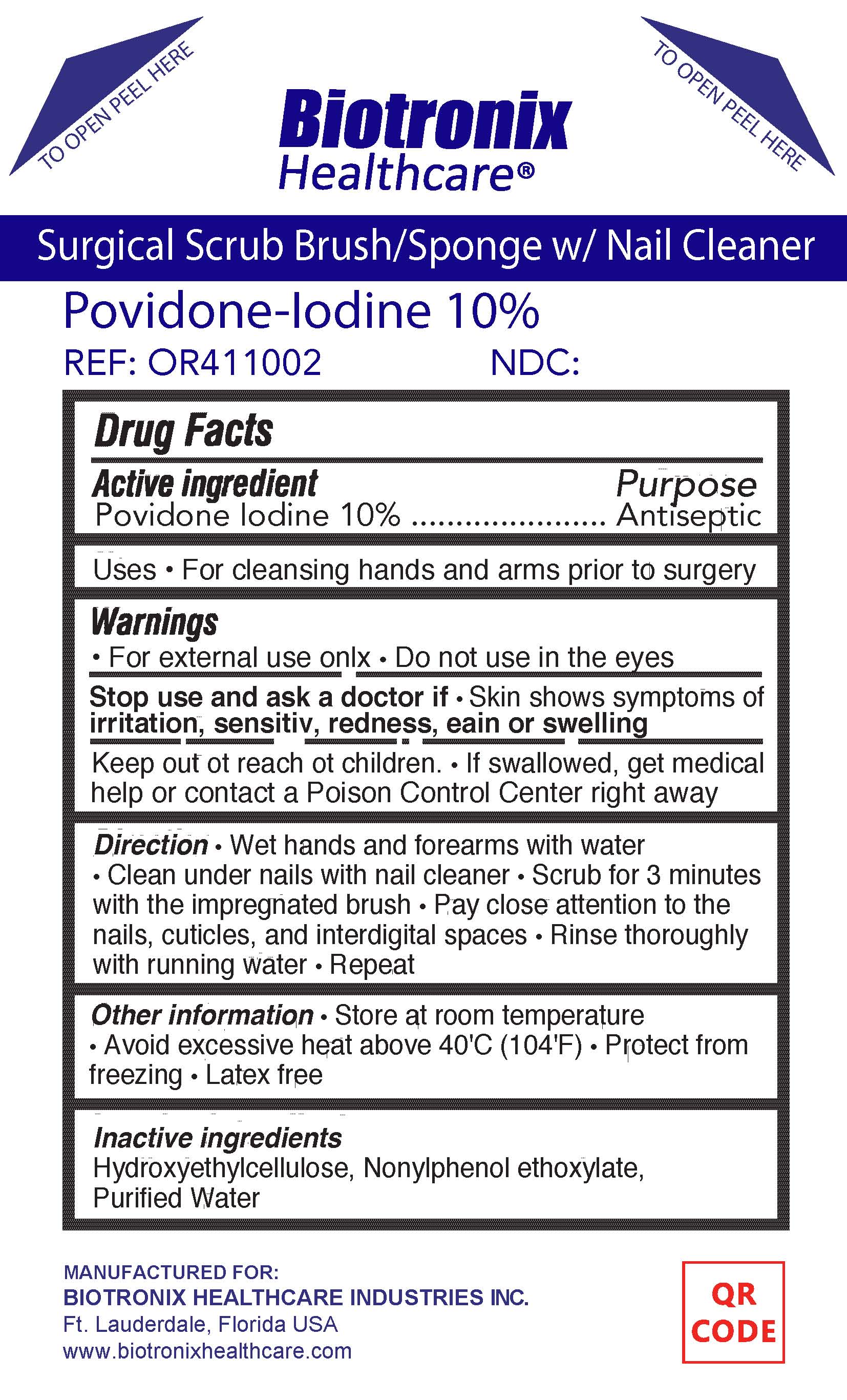 DRUG LABEL: POVIDONE IODINE SURGICAL SCRUB
NDC: 71389-102 | Form: SPONGE
Manufacturer: Biotronix Healthcare Industries, Inc.
Category: otc | Type: HUMAN OTC DRUG LABEL
Date: 20180506

ACTIVE INGREDIENTS: POVIDONE-IODINE 100 mg/1 mL
INACTIVE INGREDIENTS: WATER; HYDROXYETHYL CELLULOSE (100 MPA.S AT 2%); NONOXYNOL-10

Active ingredient

Povidone Iodine 10%

Purpose
Antiseptic

Warnings
For external use only. Do not use in the eyes.

Stop use and ask a doctor if Skin shows symptons of irritation, sensitivity, redness, pain or swelling

DOSAGE AND ADMINISTRATION

Direction

- Wet hands and forearms with water
- Clean under nails with nail cleaner
- Scrub for 3 minutes with the impregnated brush
- Pay close attention to the nails, cuticles, and interdigital spaces
- Rinse thoroughly with running water
- Repeat

Inactive ingredients

Hydroxyethylcellulose, Nonoxynol ethoxylate, Purified Water

INDICATIONS AND USAGE

Uses For cleansing hands and arms prior to surgery

Other information

- Store at room temperature
- Avoid excessive heat above 40 °C (104 °F)
- Protect from freezing
- Latex free

Keep out of reach of children. If swallowed, get medical help or contact a Poison Control Center right away.